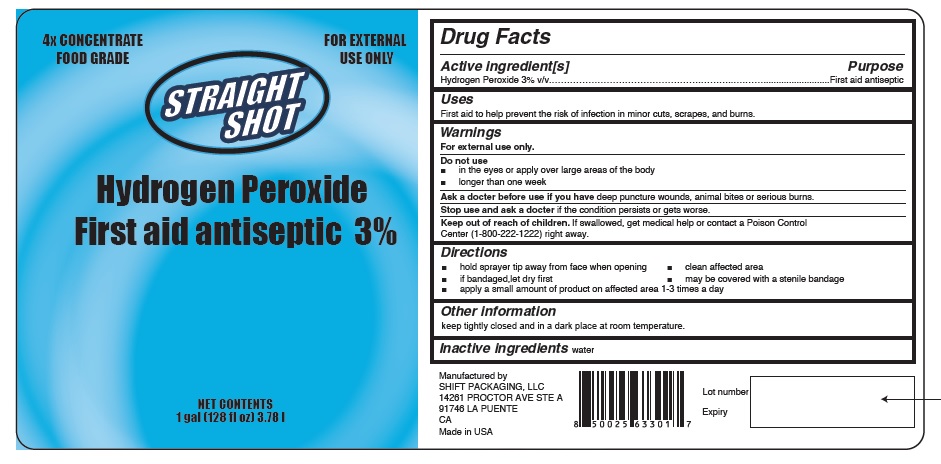 DRUG LABEL: STRAIGHT SHOT
NDC: 79170-001 | Form: LIQUID
Manufacturer: Shift Packaging, LLC
Category: otc | Type: HUMAN OTC DRUG LABEL
Date: 20201105

ACTIVE INGREDIENTS: HYDROGEN PEROXIDE 3 mL/100 mL
INACTIVE INGREDIENTS: WATER

STRAIGHT SHOT

Active Ingredients

Hydrogen Peroxide 3%

Purpose

First aid antiseptic

Uses

First aid to help prevent the risk of infection in minor cuts, scrapes, and burns.

Warnings

For external use only.

Do not use■ in the eyes or apply over large areas of the body.
■ longer than one week.

- Ask a docter before use if you have deep puncture wounds, animal bites or serious burns.
- Stop use and ask a doctor if the condition persists or gets worse.

Keep out of reach of children. If swallowed, get medical help or contact a Poison Control
Center (1-800-222-1222) right away.

Directions

■ hold sprayer tip away from face when opening.

■ clean affected area.
■ if bandaged,let dry first.

■ may be covered with a stenile bandage.
■ apply a small amount of product on affected area 1-3 times a day.

Other information

- keep tightly closed and in a dark place at room temperature.

Inactive Ingredient

water